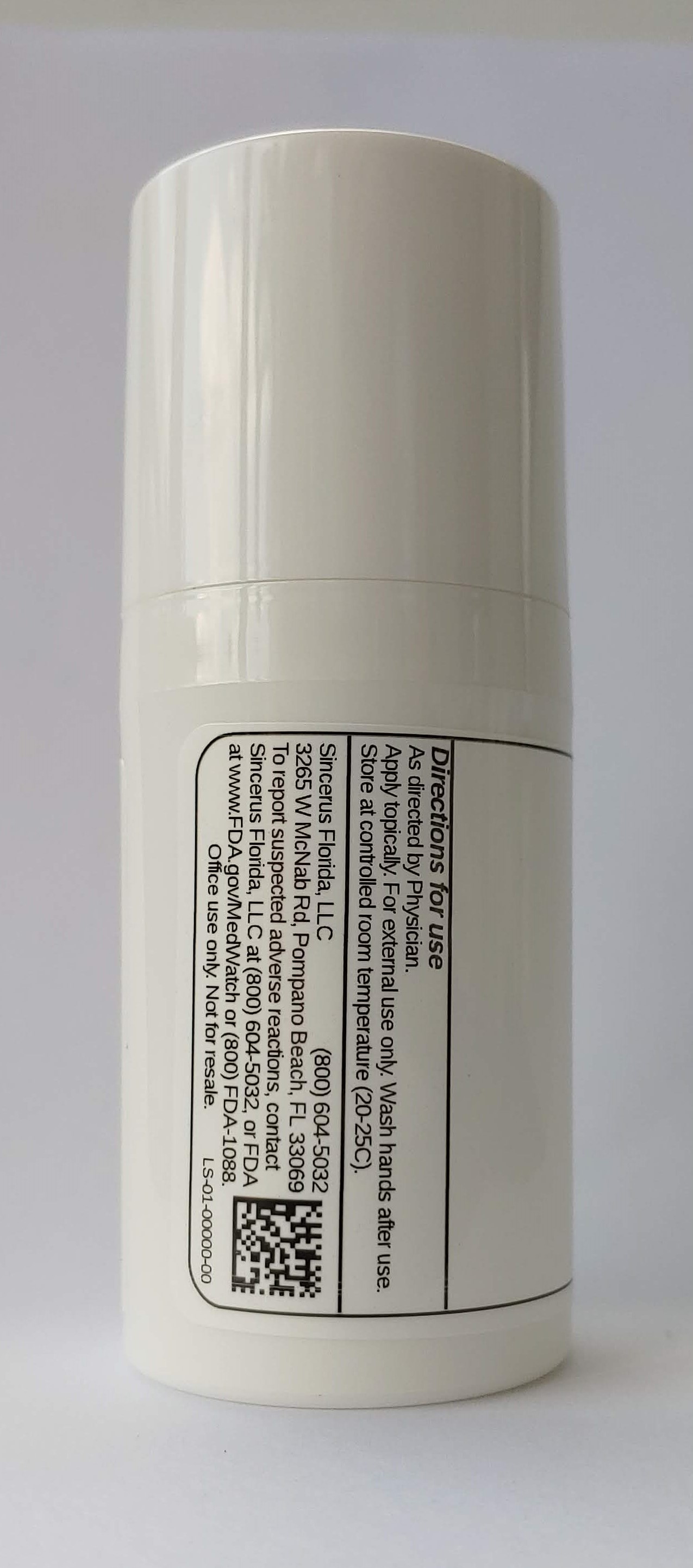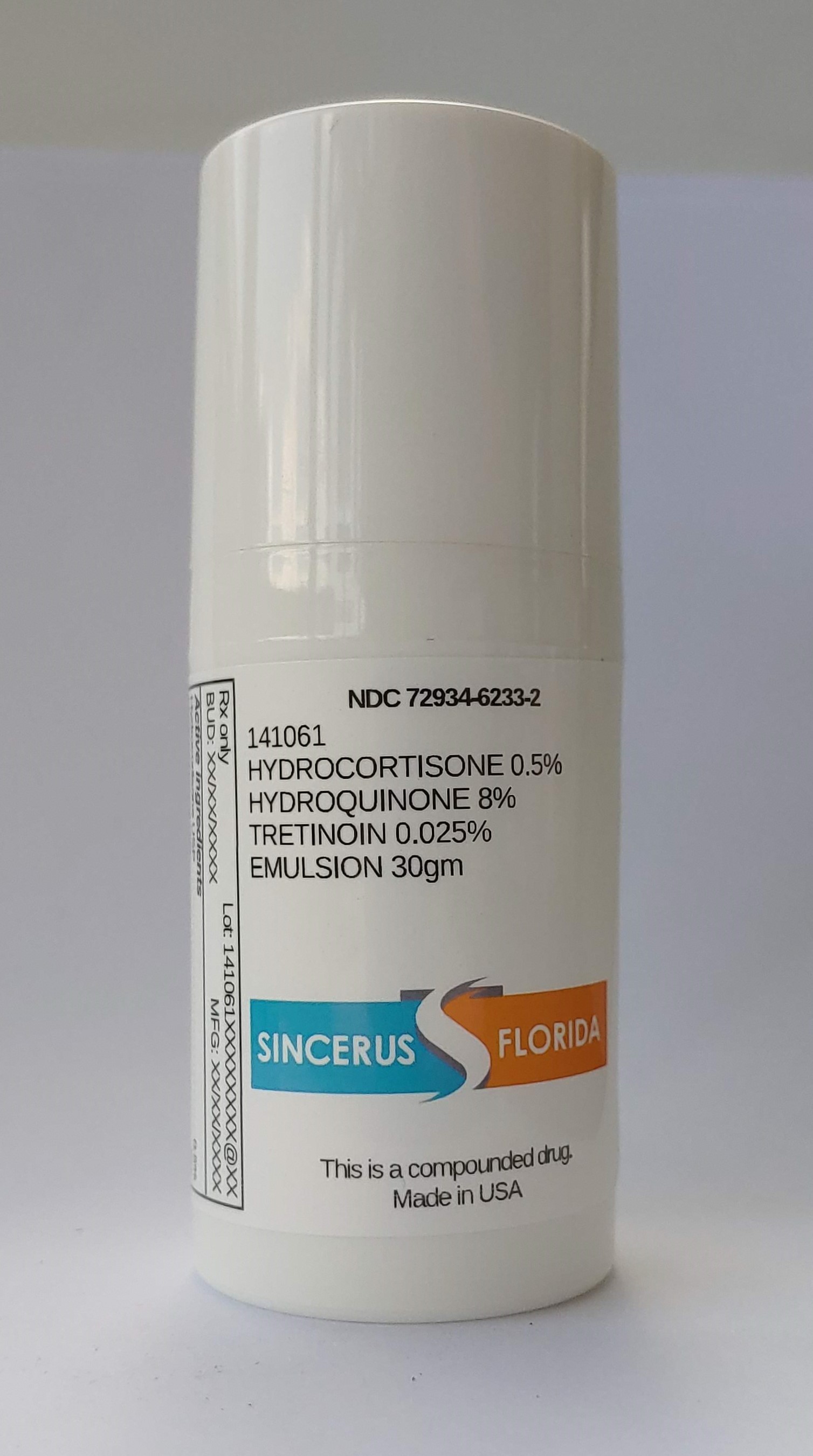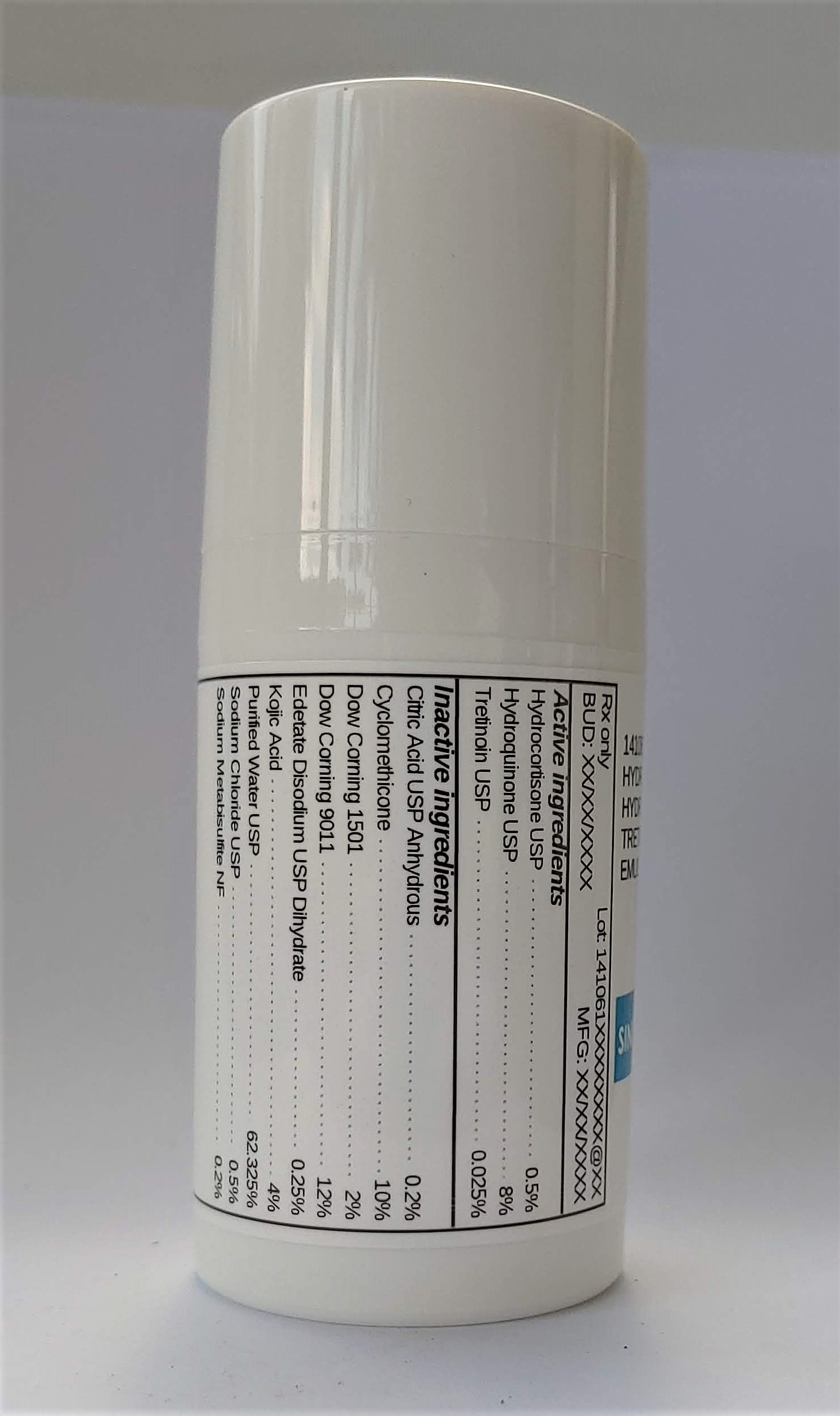 DRUG LABEL: 141061 HYDROCORTISONE 0.5% / HYDROQUINONE 8% / TRETINOIN 0.025%
NDC: 72934-6233 | Form: EMULSION
Manufacturer: Sincerus Florida, LLC
Category: prescription | Type: HUMAN PRESCRIPTION DRUG LABEL
Date: 20200702

ACTIVE INGREDIENTS: HYDROQUINONE 8 g/100 g; TRETINOIN 0.025 g/100 g; HYDROCORTISONE 0.5 g/100 g

141061 HYDROCORTISONE 0.5% / HYDROQUINONE 8% / TRETINOIN 0.025%